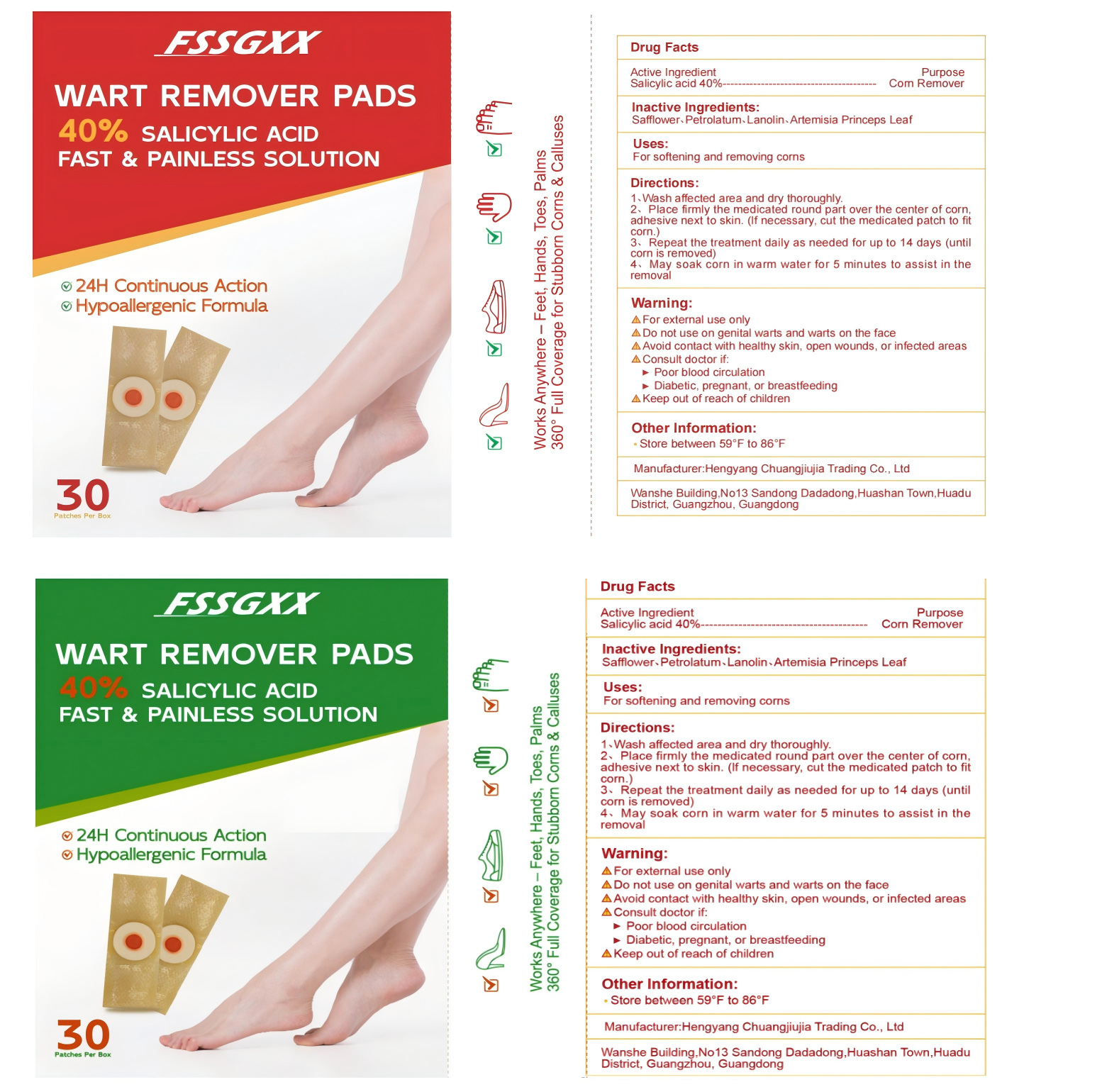 DRUG LABEL: Wart Remover Pads
NDC: 84735-005 | Form: PATCH
Manufacturer: Hengyang Chuangjiujia Trading Co., Ltd.
Category: otc | Type: HUMAN OTC DRUG LABEL
Date: 20250318

ACTIVE INGREDIENTS: SALICYLIC ACID 0.4 g/1 1
INACTIVE INGREDIENTS: SAFFLOWER; PETROLATUM; ARTEMISIA PRINCEPS LEAF; LANOLIN

Wart Remover Pads

ACTIVE INGREDIENT

Salicylic acid 40%

PURPOSE

Com Remover

INDICATIONS AND USAGE

For softening and removing corns

WARNINGS

For external use only
Do not use on genital warts and warts on the face
Avoid contact with healthy skin, open wounds, or infected areas
Consult doctor if:
Poor blood circulation
Diabetic, pregnant, or breastfeeding
Keep out of reach of children

Do not use on genital warts and warts on the face
Avoid contact with healthy skin, open wounds, or infected areas

WHEN USING

For external use only
Do not use on genital warts and warts on the face
Avoid contact with healthy skin, open wounds, or infected areas
Consult doctor if:
Poor blood circulation
Diabetic, pregnant, or breastfeeding
Keep out of reach of children

Keep out of reach of children

DOSAGE AND ADMINISTRATION

1、Wash affected area and dry thoroughly.
2、Place firmly the medicated round part over the center of cornadhesive next to skin. (lf necessary, cut the medicated patch to fitcorn.)
3、Repeat the treatment daily as needed for up to 14 days (unticorn is removed)
4、May soak corn in warm water for 5 minutes to assist in theremova

STORAGE AND HANDLING

Store between 59°F to 86°F

INACTIVE INGREDIENT

SAFFLOWER
PETROLATUM
LANOLIN
ARTEMISIA PRINCEPS LEAF